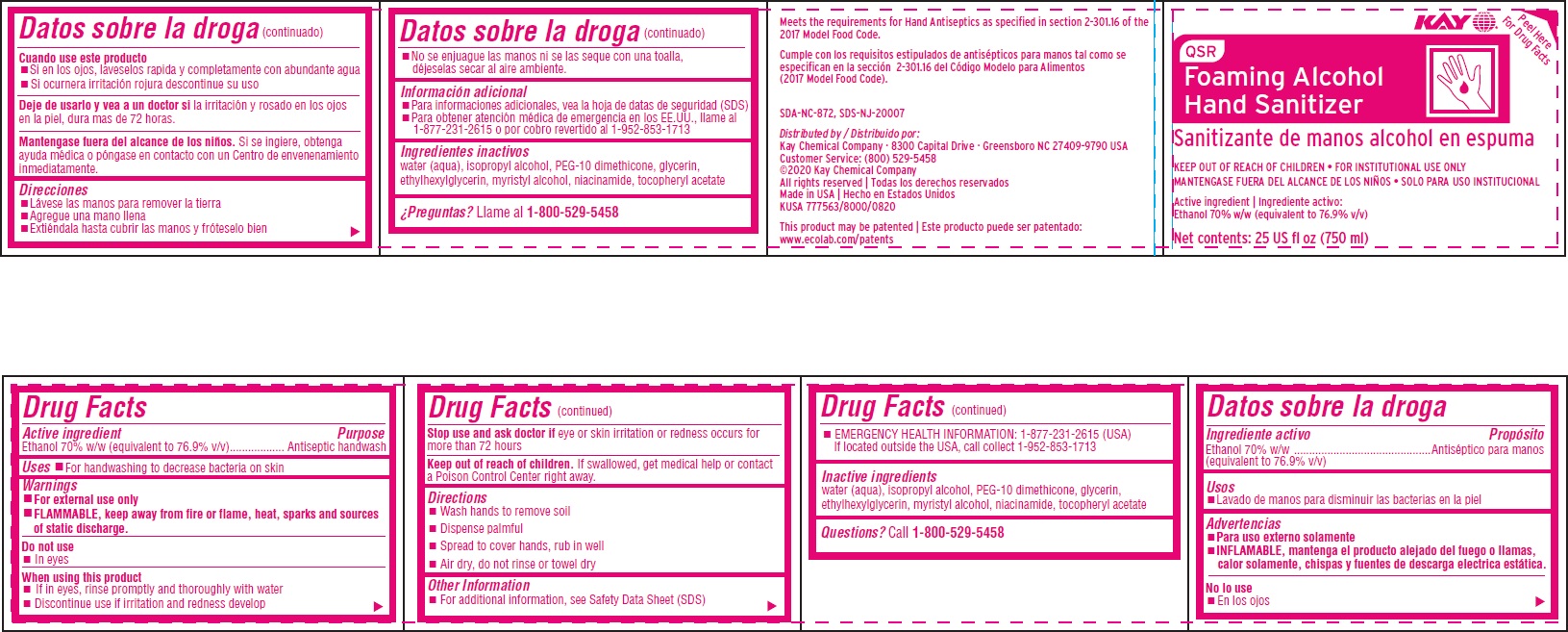 DRUG LABEL: QSR Foaming Alcohol Hand Sanitizer
NDC: 63146-310 | Form: SOLUTION
Manufacturer: Kay Chemical Company
Category: otc | Type: HUMAN OTC DRUG LABEL
Date: 20240820

ACTIVE INGREDIENTS: ALCOHOL 76.9 mL/100 mL
INACTIVE INGREDIENTS: WATER; ISOPROPYL ALCOHOL; BIS-PEG-12 DIMETHICONE (500 MPA.S); GLYCERIN; ETHYLHEXYLGLYCERIN; MYRISTYL ALCOHOL; NIACINAMIDE; .ALPHA.-TOCOPHEROL ACETATE

Drug Facts

Active Ingredient

Ethyl alcohol 70% w/w (equivalent to 76.9% v/v)

Purpose

Antiseptic handwash

Uses

- for handwashing to decrease bacteria on the skin

Warnings

- For external use only
- FLAMMABLE, keep away from fire or flame, heat, sparks and sources of static discharge

Do not use

- in eyes

When using this product

- if in eyes, rinse promptly and thoroughly with water
- discontinue use if irritation and redness develop

Stop use and ask a doctor if eye or skin irritation or redness occurs for more than 72 hours.

Keep out of reach of children. If swallowed, get medical help or contact a Poison Control Center right away.

Directions

- wash hands to remove soil
- dispense palmful
- spread to cover hands, rub in well
- air dry, do not rinse or towel dry

Other information

- for additional information, see Safety Data Sheet (SDS)
- EMERGENCY HEALTH INFORMATION: 1-877-231-2615 (USA) If located outside the USA, call collect 1-952-853-1713

INACTIVE INGREDIENT

Inactive ingredients water (aqua), isopropyl alcohol, PEG-10 dimethicone, glycerin, ethylhexylglycerin, myristyl alcohol, niacinamide, tocopheryl acetate

Questions?

Call 1-800-529-5458

Principal display panel and representative label

QSR

Foaming Alcohol

Hand Sanitizer

Sanitizante de manos alcohol en espuma

KEEP OUT OF REACH OF CHILDREN • FOR INSTITUTIONAL USE ONLY

MANTENGASE FUERA DEL ALCANCE DE LOS NIÑOS • SOLO PARA USO INSTITUCIONAL

Active ingredient | Ingrediente activo:

Ethanol 70% w/w (equivalent to 76.9% v/v)

Net contents: 25 US fl oz (750 ml)

Meets the requirements for Hand Antiseptics as specified in section 2-301.16 of the 2017 Model Food Code.

Cumple con los requisitos estipulados de antisépticos para manos tal como se especifican en la sección 2-301.16 del Código Modelo para limentos (2017 Model Food Code).

SDA-NC-872, SDS-NJ-20007

Distributed by / Distribuido por:

Kay Chemical Company · 8300 Capital Drive · Greensboro NC 27409-9790 USA Customer Service: (800) 529-5458

©2020 Kay Chemical Company

All rights reserved | Todas los derechos reservados

Made in USA | Hecho en Estados Unidos

KUSA 777563/8000/0820

This product may be patented | Este producto puede ser patentado:

www.ecolab.com/patents